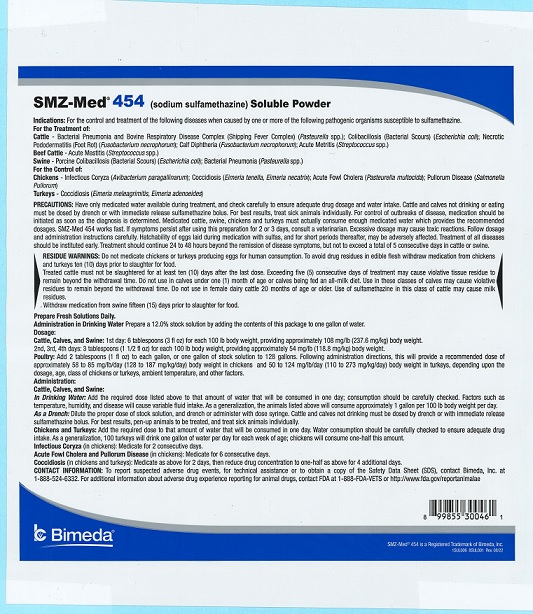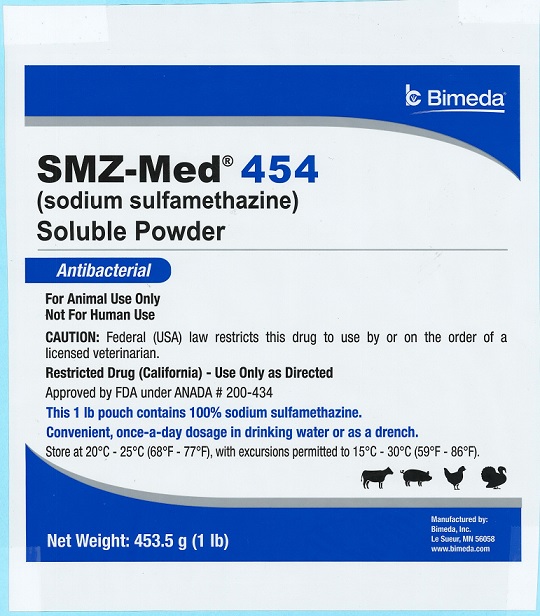 DRUG LABEL: SMZ-Med 454
NDC: 61133-8001 | Form: POWDER
Manufacturer: Bimeda, Inc.
Category: animal | Type: PRESCRIPTION ANIMAL DRUG LABEL
Date: 20240423

ACTIVE INGREDIENTS: Sulfamethazine 453.5 g/453.5 g

DESCRIPTION

SMZ-Med® 454
(sodium sulfamethazine)
Soluble Powder
Antibacterial
For Animal Use Only
Not for Human Use
CAUTION: Federal (USA) law restricts this drug to use by or on the order of a licensed veterinarian.
Restricted Drug (California) - Use Only as Directed
Approved by FDA under ANADA # 200-434

This 1 lb pouch contains 100% sodium sulfamethazine.
Convenient, once-a-day dosage in drinking water or as a drench

INDICATIONS AND USAGE

INDICATIONS:For the control and treatment of the following diseases when caused by one or more of the following pathogenic organisms susceptible to sulfamethazine.

For the Treatment of:
Cattle- Bacterial Pneumonia and Bovine Respiratory Disease Complex (Shipping Fever Complex) (Pasteurella spp.); Colibacillosis (Bacterial Scours) (Escherichia coli); Necrotic Pododermatitis (Foot Rot) (Fusobacterium necrophorum); Calf Diphtheria (Fusobacterium necrophorum); Acute Metritis (Streptococcus spp.)
Beef Cattle- Acute Mastitis (Streptococcus spp.)
Swine- Porcine Colibacillosis (Bacterial Scours) (Escherichia coli); Bacterial Pneumonia (Pasteurella spp.)
For the Control of:
Chickens - Infectious Coryza (Avibacterium paragallinarum); Coccidiosis (Eimeria tenella, Eimeria necatrix); Acute Fowl Cholera (Pasteurella multocida); Pullorum Disease (Salmonella Pullorum)
Turkeys- Coccidiosis (Eimeria meleagrimitis, Eimeria adenoeides)

WARNINGS AND PRECAUTIONS

RESIDUE WARNINGS: Do not medicate chickens or turkeys producing eggs for human consumption. To avoid drug residues in edible flesh withdraw medication from chickens and turkeys ten (10) days prior to slaughter for food.

Treated cattle must not be slaughtered for at least ten (10) days after the last dose. Exceeding five (5) consecutive days of treatment may cause violative tissue residue to remain beyond the withdrawal time. Do not use in calves under one (1) month of age or calves being fed an all-milk diet. Use in these classes of calves may cause violative residues to remain beyond the withdrawal time. Do not use in female dairy cattle 20 months of age or older. Use of sulfamethazine in this class of cattle may cause milk residues. Withdraw medication from swine fifteen (15) days prior to slaughter for food.

PRECAUTIONS: Have only medicated water available during treatment, and check carefully to ensure adequate drug dosage and water intake. Cattle and calves not drinking or eating must be dosed by drench or with immediate release sulfamethazine bolus. For best results, treat sick animals individually. For control of outbreaks of disease, medication should be initiated as soon as the diagnosis is determined. Medicated cattle, swine, chickens and turkeys must actually consume enough medicated water which provides the recommended dosages. SMZ-Med 454 works fast. If symptoms persist after using this preparation for 2 or 3 days, consult a veterinarian. Excessive dosage may cause toxic reactions. Follow dosage and administration instructions carefully. Hatchability of eggs laid during medication of sulfas, and for short periods thereafter, may be adversely affected. Treatment of all diseases should be instituted early. Treatment should continue 24 to 48 hours beyond the remission of disease symptoms, but not to exceed a total of 5 consecutive days in cattle or swine.

The Safety Data Sheet (SDS) contains more detailed occupational safety information. To report adverse drug events, for technical assistance or to obtain a copy of the SDS, contact Bimeda, Inc. at 1-888-524-6332. For additional information about adverse drug experience reporting for animal drugs, contact FDA at 1-888-FDA-VETS or online at www.fda.gov/reportanimalae.

DOSAGE AND ADMINISTRATION

Prepare Fresh Solutions Daily.
Administration in Drinking Water Prepare a 12.0% stock solution by adding the contents of this package to one gallon of water.

Dosage:
Cattle, Calves and Swine
1st day: 6 tablespoons (3 fl oz) for each 100 lb body weight, providing approximately 108 mg/lb (237.6 mg/kg) body weight.
2nd, 3rd, 4th days: 3 tablespoons (1 1/2 fl oz) for each 100 lb body weight, providing approximately 54 mg/lb (118.8 mg/kg) body weight.

Poultry: Add 2 tablespoons (1 fl oz) to each gallon, or one gallon of stock solution to 128 gallons. Following administration directions, this will provide a recommended dose of approximately 58 to 85 mg/lb/day (128 to 187 mg/kg/day) body weight in chickens and 50 to 124 mg/lb/day (110 to 273 mg/kg/day) body weight in turkeys, depending upon the dosage, age, class of chickens or turkeys, ambient temperature and other factors.

Administration:
Cattle, Calves, and Swine:

In Drinking Water: Add the required dose listed above to that amount of water that will be consumed in one day; consumption should be carefully checked. Factors such as temperature, humidity and disease will cause variable fluid intake. As a generalization, the animals listed above will consume approximately 1 gallon per 100 lb body weight per day.

As a Drench: Dilute the proper dose of stock solution, and drench or administer with dose syringe. Cattle and calves not drinking must be dosed by drench or with immediate release sulfamethazine bolus. For best results, pen-up animals to be treated, and treat sick animals individually.

Chickens and Turkeys: Add the required dose to that amount of water that will be consumed in one day. Water consumption should be carefully checked to ensure adequate drug intake. As a generalization, 100 turkeys will drink one gallon of water per day for each week of age; chickens will consume one-half this amount.

Infectious Coryza (in chickens): Medicate for 2 consecutive days.

Acute Fowl Cholera and Pullorum Disease (in chickens): Medicate for 6 consecutive days.

Coccidiosis (in chickens and turkeys): Medicate as above for 2 days, then reduce drug concentration to one-half as above for 4 additional days.

STORAGE AND HANDLING

Store at 20°C - 25°C (68°F - 77°F), with excursions permitted to 15°C - 30°C (59°F - 86°F).